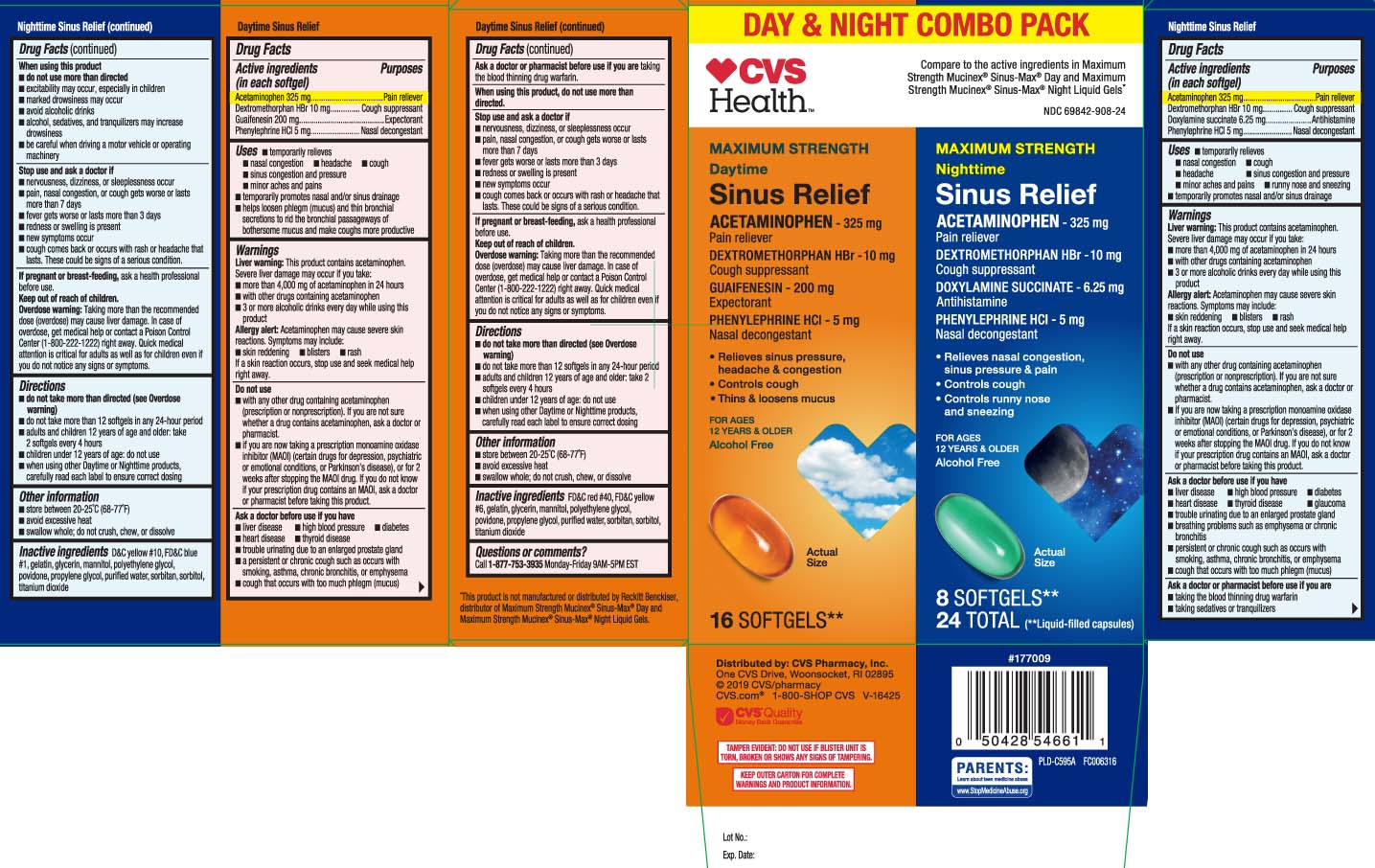 DRUG LABEL: Daytime Nighttime Sinus Relief
NDC: 69842-908 | Form: KIT | Route: ORAL
Manufacturer: CVS Pharmacy
Category: otc | Type: HUMAN OTC DRUG LABEL
Date: 20250818

ACTIVE INGREDIENTS: ACETAMINOPHEN 325 mg/1 1; DEXTROMETHORPHAN HYDROBROMIDE 10 mg/1 1; DOXYLAMINE SUCCINATE 6.25 mg/1 1; PHENYLEPHRINE HYDROCHLORIDE 5 mg/1 1; ACETAMINOPHEN 325 mg/1 1; DEXTROMETHORPHAN HYDROBROMIDE 10 mg/1 1; PHENYLEPHRINE HYDROCHLORIDE 5 mg/1 1; GUAIFENESIN 200 mg/1 1
INACTIVE INGREDIENTS: D&C YELLOW NO. 10; FD&C BLUE NO. 1; GELATIN; GLYCERIN; POLYETHYLENE GLYCOL, UNSPECIFIED; POVIDONE; PROPYLENE GLYCOL; WATER; SORBITAN; SORBITOL; TITANIUM DIOXIDE; MANNITOL; FD&C RED NO. 40; FD&C YELLOW NO. 6; GELATIN; GLYCERIN; POLYETHYLENE GLYCOL, UNSPECIFIED; POVIDONE; PROPYLENE GLYCOL; WATER; SORBITAN; SORBITOL; TITANIUM DIOXIDE; MANNITOL

Drug Facts

Active ingredients in Daytime (in each softgel)

Acetaminophen 325 mg

Dextromethorphan HBr 10 mg

Guaifenesin 200 mg

Phenylephrine HCl 5 mg

Active ingredients in Nighttime (in each softgel)

Acetaminophen 325 mg

Dextromethorphan HBr 10 mg

Doxylamine succinate 6.25 mg

Phenylephrine HCI 5 mg

Purpose for Daytime

Pain reliever

Cough suppressant

Expectorant

Nasal decongestant

Purpose for Nighttime

Pain reliever

Cough suppressant

Antihistamine

Nasal decongestant

Uses

DAYTIME

- temporarily relieves
  - nasal congestion
  - headache
  - cough
  - sinus congestion and pressure
  - minor aches and pains
  - temporarily promotes nasal and/or sinus drainage
  - helps loosen phlegm (mucus) and thin bronchial secretions to rid the bronchial passageways of bothersome mucus and make coughs more productive

NIGHTTIME

- temporarily relieves
  - nasal congestion
  - cough
  - headache
  - sinus congestion and pressure
  - minor aches and pains
  - runny nose and sneezing
- temporarily promotes nasal and/or sinus drainage

Warnings

DAYTIME and NIGHTTIME

Liver warning: These products contain acetaminophen. Severe liver damage may occur if you take:

- more than 4,000 mg of acetaminophen in 24 hours
- with other drugs containing acetaminophen
- 3 or more alcoholic drinks every day while using this product

Allergy alert: Acetaminophen may cause severe skin reactions. Symptoms may include:

- skin reddening
- blisters
- rash

If a skin reaction occurs, stop use and seek medical help right away

Do not use

DAYTIME and NIGHTTIME

- with any other drug containing acetaminophen (prescription or nonprescription). If you are not sure whether a drug contains acetaminophen, ask a doctor or pharmacist.
- if you are now taking a prescription monoamine oxidase inhibitor (MAOI) (certain drugs for depression, psychiatric or emotional conditions, or Parkinson’s disease), or for 2 weeks after stopping the MAOI drug. If you do not know if your prescription drug contains an MAOI, ask a doctor or pharmacist before taking this product.

Ask a doctor before use if you have

DAYTIME

- liver disease
- high blood pressure
- diabetes
- heart disease
- thyroid disease
- trouble urinating due to an enlarged prostate gland
- a persistent or chronic cough such as occurs with smoking, asthma, chronic bronchitis, or emphysema
- cough that occurs with too much phlegm (mucus)

NIGHTTIME

- liver disease
- high blood pressure
- diabetes
- heart disease
- thyroid disease
- glaucoma
- trouble urinating due to an enlarged prostate gland
- breathing problem s such as emphysema or chronic bronchitis
- persistent or chronic cough such as occurs with smoking, asthma, chronic bronchitis, or emphysema
- cough that occurs with too much phlegm (mucus)

Ask a doctor or pharmacist before use if you are

DAYTIME

taking the blood thinning drug warfarin

NIGHTTIME

- taking the blood thinning drug warfarin
- taking sedatives or tranquilizers

When using this product,

DAYTIME

do not use more than directed

NIGHTTIME

- do not use more than directed
- excitability may occur, especially in children
- marked drowsiness may occur
- avoid alcoholic drinks
- alcohol, sedatives, and tranquilizers may increase drowsiness
- be careful when driving a motor vehicle or operating machinery

Stop use and ask a doctor if

DAYTIME and NIGHTTIME

- nervousness, dizziness, or sleeplessness occur
- pain, nasal congestion, or cough gets worse or lasts more than 7 days
- fever gets worse or lasts more than 3 days
- redness or swelling is present
- new symptoms occur
- cough comes back or occurs with rash or headache that lasts. These coukld be signs of a serious condition.

If pregnant or breast-feeding,

DAYTIME and NIGHTTIME

ask a health professional before use.

Keep out of reach of children.

DAYTIME and NIGHTTIME

Overdose warning: Taking more than the recommended dose can cause liver damage. In case of overdose, get medical help or contact a Poison Control Center (1-800-222-1222) right away. Quick medical attention is critical for adults as well as for children even if you do not notice any signs or symptoms.

Directions

DAYTIME

- do not take more than directed (see Overdose warning)
- do not take more than 12 softgels in any 24-hour period
- adults and children 12 years of age and older: take 2 softgels every 4 hours
- children under 12 years of age: do not use
- when using other Daytime or Nighttime products, carefully read each label to ensure correct dosing

NIGHTTIME

- do not take more than directed (see Overdose warning)
- do not take more than 12 softgels in any 24-hour period
- adults and children 12 years of age and older: take 2 softgels every 4 hours
- children under 12 years of age: do not use
- when using other Daytime or Nighttime products, carefully read each label to ensure correct dosing

Other information

DAYTIME and NIGHTTIME

- swallow whole; do not crush, chew, or dissolve
- store between 15-30ºC (59-86F)
- avoid excessive heat

Inactive ingredients

DAYTIME

FD&C red #40, FD&C yellow #6, gelatin, glycerin, mannitiol, polyethylene glycol, povidone, propylene glycol, purified water, sorbitan, sorbitol, titanium dioxide

NIGHTTIME

D&C yellow #10, FD&C blue #1, gelatin, glycerin, mannitol, polyethylene glycol, povidone, propylene glycol, purified water, sorbitan, sorbitol, titanium dioxide

Questions or comments?

DAYTIME and NIGHTTIME

Call 1-877-753-3935 Monday-Friday 9AM-5PM EST

Principal Display Panel

Compare to the active ingredients Maximum Strength Mucinex® Sinus-Max® Day and Maximum Strength Mucinex® Sinus-Max® Night Liquid Gel*

MAXIMUM STRENGTH

DAYTIME

Sinus Relief

ACETAMINOPHEN - 325 mg Pain reliever

DEXTROMETHORPHAN HBr - 10 mg Cough suppressant

GUAIFENESIN - 200 mg Expectorant

PHENYLEPHRINE HCL - 5 mg Nasal decongestant

- Relieves sinus pressure, headache & congestion
- Controls cough
- thins & loosens mucus

FOR AGES 12 YEARS & OLDER

Alcohol Free

SOFTGELS**

MAXIMUM STRENGTH

NIGHTTIME

Sinus Relief

ACETAMINOPHEN - 325 mg Pain reliever

DEXTROMETHORPHAN HBr - 10 mg Cough suppressant

DOXYLAMINE SUCCINATE - 6.25 mg Antihistamine

PHENYLEPHRINE HCL - 5 mg Nasal decongestant

- Relieves nasal congestion, sinus pressure & pain
- Controls cough
- Controls runny nose and sneezing

FOR AGES 12 YEARS & OLDER

Alcohol Free

SOFTGELS*

(**Liquid-filled capsules)

*This product is not manufactured or distributed by Reckitt Benckiser, distributor of Maximum Strength Mucinex® Sinus-Max® Day and Maximum Strength Mucinex® Sinus-Max® Night.Liquid Gels.

TAMPER EVIDENT: DO NOT USE IF BLISTER UNIT IS TORN, BROKEN OR SHOWS ANY SIGNS OF TAMPERING

KEEP OUTER CARTON FOR COMPLETE WARNINGS AND PRODUCT INFORMATION.

Distributed by: CVS Pharmacy, Inc.

One CVS Drive, Woonsocket, RI 02895

Product Label

CVS HEALTH Maximum Strength Daytime Nighttime Sinus Relief